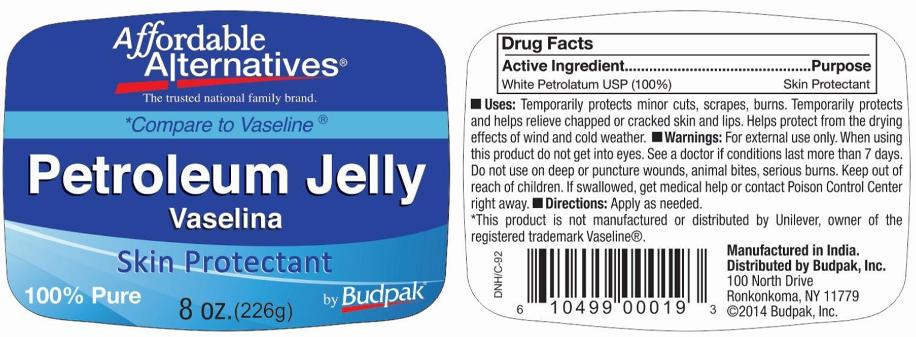 DRUG LABEL: Budpak Petroleum
NDC: 27293-033 | Form: JELLY
Manufacturer: Budpak Inc.
Category: otc | Type: HUMAN OTC DRUG LABEL
Date: 20140707

ACTIVE INGREDIENTS: PETROLATUM 100 g/100 g

BUDPAK PETROLEUM JELLY

Active Ingredient

White Petrolatum USP (100%)

Purpose

Skin Protectant

Uses

- Temporarily protects minor cuts, scrapes or burns.
- Temporarily protects and helps relieve chapped or cracked skin and lips.
- Helps protect from the drying effects of wind and cold weather.

Warnings

For external use only.

When using this product do not get into eyes.

Stop use and ask a doctor if

• conditions last more than 7 days.

Do not use on

- deep or puncture wounds
- animal bites
- serious burns

Keep out of reach of children

- If swallowed, get medical help or contact a Poison Control Center right away.

Directions

Apply as needed.

Inactive Ingredients

None

PRINCIPAL DISPLAY PANEL

BUDPAK PETROLEUM JELLY

NET WT. 8 OZ. (226g)